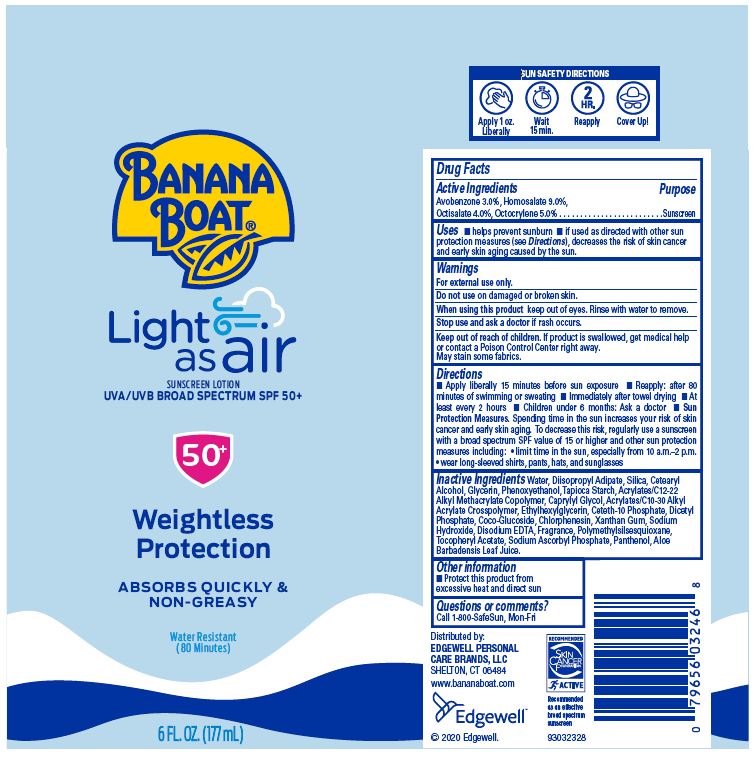 DRUG LABEL: Banana Boat
NDC: 63354-481 | Form: LOTION
Manufacturer: Edgewell Personal Care Brands, LLC
Category: otc | Type: HUMAN OTC DRUG LABEL
Date: 20241125

ACTIVE INGREDIENTS: OCTISALATE 4 g/100 g; AVOBENZONE 3 g/100 g; HOMOSALATE 9 g/100 g; OCTOCRYLENE 5 g/100 g
INACTIVE INGREDIENTS: CETOSTEARYL ALCOHOL; CHLORPHENESIN; POLYMETHYLSILSESQUIOXANE (11 MICRONS); ETHYLHEXYLGLYCERIN; COCO GLUCOSIDE; SODIUM HYDROXIDE; SODIUM ASCORBYL PHOSPHATE; ALOE VERA LEAF; SILICON DIOXIDE; GLYCERIN; PHENOXYETHANOL; DIISOPROPYL ADIPATE; STARCH, TAPIOCA; CAPRYLYL GLYCOL; PANTHENOL; WATER; CARBOMER INTERPOLYMER TYPE A (ALLYL SUCROSE CROSSLINKED); CETETH-10 PHOSPHATE; DIHEXADECYL PHOSPHATE; XANTHAN GUM; EDETATE DISODIUM; .ALPHA.-TOCOPHEROL ACETATE

Active Ingredient

Avobenzone 3.0%, Homosalate 9.0%, Octisalate 4.0%, Octocrylene 5.0%

Purpose

Sunscreen

Uses

Helps prevent sunburn.

If used as directed with other sun protection measures (see Directions), decreases the risk of skin cancer and early skin aging caused by the sun.

Warnings

For external use only

May stain some fabrics.

Do not use

on damaged or broken skin

When using this product

keep out of eyes. Rinse with water to remove.

Stop use and ask a doctor

if rash occurs.

Keep out of reach of children

If product is swallowed, get medical help or contact a Poison Control Center right away.

Directions

Apply liberally 15 minutes before sun exposure • Reapply: after 80 minutes of swimming or sweating • Immediately after towel drying • At least every 2 hours • Children under 6 months: Ask a doctor • Sun Protection Measures. Spending time in the sun increases your risk of skin cancer and early skin aging. To decrease this risk, regularly use a sunscreen with a broad spectrum SPF value of 15 or higher and other sun protection measures including: • limit time in the sun, especially from 10 a.m. - 2 p.m. • wear long-sleeved shirts,pants, hats, and sunglasses

Inactive Ingredients

Water, Diisopropyl Adipate, Silica, Cetearyl Alcohol, Glycerin, Phenoxyethanol, Tapioca Starch, Acrylates/C12-22 Alkyl Methacrylate Copolymer, Caprylyl Glycol, Acrylates/C10-30 Alkyl Acrylate Crosspolymer, Ethylhexlyglycerin, Ceteth-10 Phosphate, Dicetyl Phosphate, Coco-Glucoside, Chlorphenesin, Xanthan Gum, Sodium Hydroxide, Disodium EDTA, Fragrance, Polymethylsilsesquioxane, Tocopheryl Acetate, Sodium Ascorbyl Phosphate, Panthenol, Aloe Barbadensis Leaf Juice

Other Information

Protect this product from excessive heat and direct sun.

Questions or Comments?

Call 1-800-SafeSun, Mon-Fri

Principal Display Panel

BANANA BOAT®
Light as air
SUNSCREEN LOTION
UVA/UVB BROAD SPECTRUM SPF 50+
50+
Weightless
Protection
ABSORBS QUICKLY &
NON-GREASY
Water Resistant
(80 Minutes)
6 FL.OZ. (177 mL)